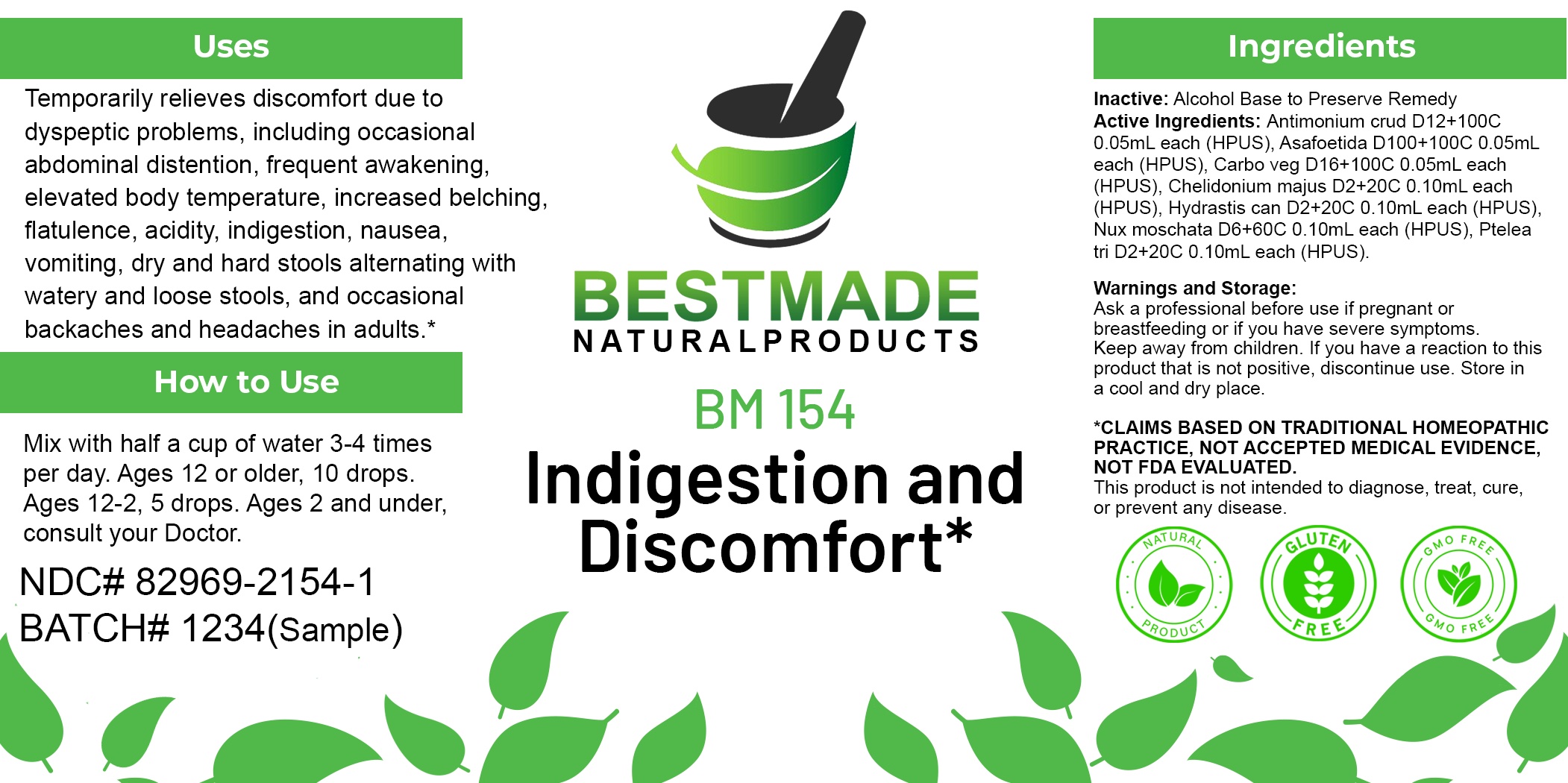 DRUG LABEL: Bestmade Natural Products BM154
NDC: 82969-2154 | Form: LIQUID
Manufacturer: Bestmade Natural Products
Category: homeopathic | Type: HUMAN OTC DRUG LABEL
Date: 20250218

ACTIVE INGREDIENTS: ANTIMONY TRISULFIDE 30 [hp_C]/30 [hp_C]; GOLDENSEAL 30 [hp_C]/30 [hp_C]; ACTIVATED CHARCOAL 30 [hp_C]/30 [hp_C]; PTELEA TRIFOLIATA BARK 30 [hp_C]/30 [hp_C]; CHELIDONIUM MAJUS 30 [hp_C]/30 [hp_C]; ASAFETIDA 30 [hp_C]/30 [hp_C]; NUTMEG 30 [hp_C]/30 [hp_C]
INACTIVE INGREDIENTS: ALCOHOL 30 [hp_C]/30 [hp_C]

BM154

DOSAGE AND ADMINISTRATION

How to Use

Mix with half a cup of water 3-4 times per day. Ages 12 or older, 10 drops. Ages 12-2, 5 drops. Ages 2 and under, consult your Doctor.

Inactive:

Alcohol Base to Preserve Product

ACTIVE INGREDIENT

Active Ingredients: Antimonium crud D12+100C 0.05mL each (HPUS), Asafoetida D100+100C 0.05mL each (HPUS), Carbo veg D16+100C 0.05mL each (HPUS), Chelidonium majus D2+20C 0.10mL each (HPUS), Hydrastis can D2+20C 0.10mL each (HPUS), Nux moschata D6+60C 0.10mL each (HPUS), Ptelea tri D2+20C 0.10mL each (HPUS).

Uses

Temporarily relieves discomfort due to dyspeptic problems, including occasional abdominal distention, frequent awakening, elevated body temperature, increased belching, flatulence, acidity, indigestion, nausea, vomiting, dry and hard stools alternating with watery and loose stools, and occasional backaches and headaches in adults.*

*CLAIMS BASED ON TRADITIONAL HOMEOPATHIC PRACTICE, NOT ACCEPTED MEDICAL EVIDENCE NOT FDA EVALUATED.

This product is not intended to diagnose, treat, cure, or prevent any disease.

Uses

Temporarily relieves discomfort due to dyspeptic problems, including occasional abdominal distention, frequent awakening, elevated body temperature, increased belching, flatulence, acidity, indigestion, nausea, vomiting, dry and hard stools alternating with watery and loose stools, and occasional backaches and headaches in adults.*

*CLAIMS BASED ON TRADITIONAL HOMEOPATHIC PRACTICE, NOT ACCEPTED MEDICAL EVIDENCE NOT FDA EVALUATED.

This product is not intended to diagnose, treat, cure, or prevent any disease.

KEEP OUT OF REACH OF CHILDREN

Warnings and Storage:

Ask a professional before use if pregnant or breastfeeding or if you have severe symptoms. Keep away from children. If you have a reaction to this product that is not positive, discontinue use. Store in a cool and dry place.

Warnings and Storage:

Ask a professional before use if pregnant or breastfeeding or if you have severe symptoms. Keep away from children. If you have a reaction to this product that is not positive, discontinue use. Store in a cool and dry place.

*CLAIMS BASED ON TRADITIONAL HOMEOPATHIC PRACTICE, NOT ACCEPTED MEDICAL EVIDENCE NOT FDA EVALUATED.

This product is not intended to diagnose, treat, cure, or prevent any disease.

Entire package label